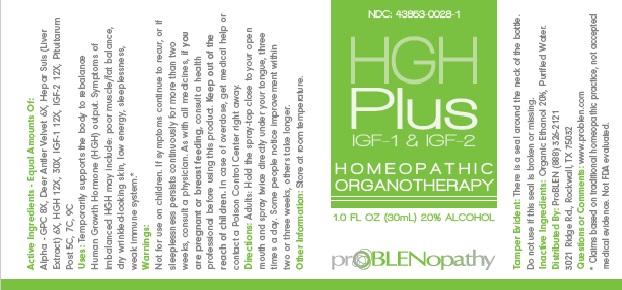 DRUG LABEL: HGH Plus
NDC: 43853-0028 | Form: SPRAY
Manufacturer: ProBlen
Category: homeopathic | Type: HUMAN OTC DRUG LABEL
Date: 20211025

ACTIVE INGREDIENTS: ALPHA 8 [hp_X]/30 mL; CERVUS ELAPHUS VELVET 6 [hp_X]/30 mL; PORK LIVER 6 [hp_X]/30 mL; SOMATROPIN 12 [hp_X]/30 mL; DALOTUZUMAB 12 [hp_X]/30 mL; INSULIN-LIKE GROWTH FACTOR-2 12 [hp_X]/30 mL; SUS SCROFA PITUITARY GLAND, POSTERIOR 5 [hp_C]/30 mL
INACTIVE INGREDIENTS: ALCOHOL; WATER

HGH Plus

ACTIVE INGREDIENT

Active Ingredients - Equal Amounts Of: Alpha - GPC 8X, Deer Antler Velvet 6X, Hepar Suis (Liver Extract) 6X, HGH 12X, 30X, IGF-1 12X, IGF-2 12X, Pituitarum Post 5C, 7C, 9C

* Claims based on traditional homeopathic practice, not accepted medical evidence. Not FDA evaluated.

INDICATIONS AND USAGE

Directions: Adults: Hold the spray-top close to your open mouth and spray twice directly under your tongue, three times a day. Some people notice improvement within two or three weeks, others take longer.

WARNINGS

Warnings: Not for use on children. If symptoms continue to recur, or if sleeplessness persists continuously for more than two weeks, consult a physician. Insomnia may be a symptom of a serious underlying medical illness. As with all medicines, if you are pregnant or breast feeding, consult a health professional before using this product. Keep out of the reach of children. In case of overdose, get medical help or contact a Poison Control Center right away.

Keep out of the reach of children.

DOSAGE AND ADMINISTRATION

Directions: Adults: Hold the spray-top close to your open mouth and spray twice directly under your tongue, three times a day.

Some people notice improvement within two or three weeks, others take longer.

Other Information: Store at room temperature.

Tamper Evident: There is a seal around the neck of the bottle. Do not use if this seal is broken or missing.

Inactive Ingredients: Organic Ethanol 20%, Purified Water.

QUESTIONS

Distributed By: ProBLEN (888) 326-2121
3021 Ridge Rd., Rockwall, TX 75032

Questions or Comments: www.problen.com

PACKAGE LABEL

NDC: 43853-0028-1

HGH Plus

IGF-1 & IGF-2

HOMEOPATHIC

ORGANOTHERAPY

1.0 FL OZ (30mL) 20% ALCOHOL

prOBLENopathy

PURPOSE

Temporarily supports the body to rebalance Human Growth Hormone (HGH) output. Symptoms of imbalanced HGH may include: poor muscle/fat balance, dry wrinkled-looking skin, low energy, sleeplessness, weak immune system.*